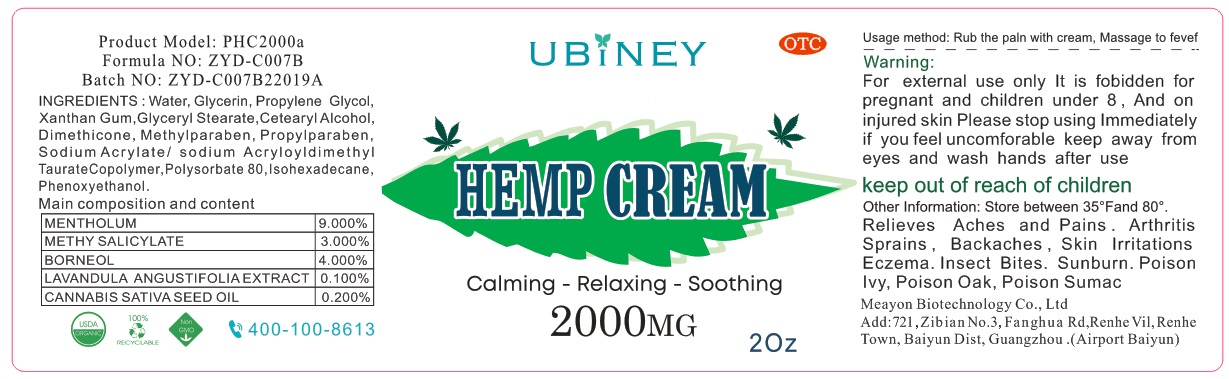 DRUG LABEL: HEMP Cream
NDC: 75728-003 | Form: CREAM
Manufacturer: Guangzhou Meayon Biotechnology Co,.Ltd
Category: otc | Type: HUMAN OTC DRUG LABEL
Date: 20220223

ACTIVE INGREDIENTS: METHYL SALICYLATE 3 mg/100 mg; MENTHOL, UNSPECIFIED FORM 9 mg/100 mg
INACTIVE INGREDIENTS: METHYLPARABEN; SODIUM ACRYLOYLDIMETHYLTAURATE; POLYSORBATE 80; WATER; GLYCERIN; BORNEOL; CANNABIS SATIVA SEED OIL; PROPYLENE GLYCOL; GLYCERYL MONOSTEARATE; DIMETHICONE; PROPYLPARABEN; SODIUM ACRYLATE; ISOHEXADECANE; PHENOXYETHANOL; CARAMEL; LAVANDULA ANGUSTIFOLIA FLOWERING TOP; XANTHAN GUM; CETOSTEARYL ALCOHOL

75728-003
75728-001 replaced by 75728-003
HEMP CREAM

Active Ingredient(s)

MENTHOLUM 9.000%
METHYL SALICYLATE 3.000%

Purpose

Rub the pain with cream, Massage to fevef

Use

Usage method: Rub the pain with cream, Massage to fevef

Warnings

Warning:
For external use only It is fobidden for pregnant and children under 8, And on injured skin
Please stop using lmmedliately if you feel uncomforable

keep away from eyes and wash hands after use

keep out of reach of children

Do not use

/

Please stop using lmmedliately if you feel uncomforable

keep away from eyes and wash hands after use

keep out of reach of children

Please stop using lmmedliately if you feel uncomforable

keep out of reach of children

Directions

Relieves Aches and Pains . Arthritis Sprains, Backaches, Skin lrritations Eczema. Insect Bites. Sunburn. Poison lvy, Poison Oak, Poison Sumac

Other information

Store between 35° Fand 80° .

Inactive ingredients

BORNEOL, LAVANDULA ANGUSTIFOLIA EXTRACT, CANNABIS SATIVA SEED OIL, Water, GLYCERIN, PROPYLENE GLYCOL, XANTHAN GUM, GLYCERYL STEARATE, CETEARYL ALCOHOL, DIMETHICONE, METHYLPARABEN, PROPYLPARABEN, SODIUM ACRYLATE, SODIUM ACRYLOYLDIMETHYL TAURATE COPOLYMER, POLYSORBATE 80, ISOHEXADECANE, PHENOXYETHANOL, CARAMEL